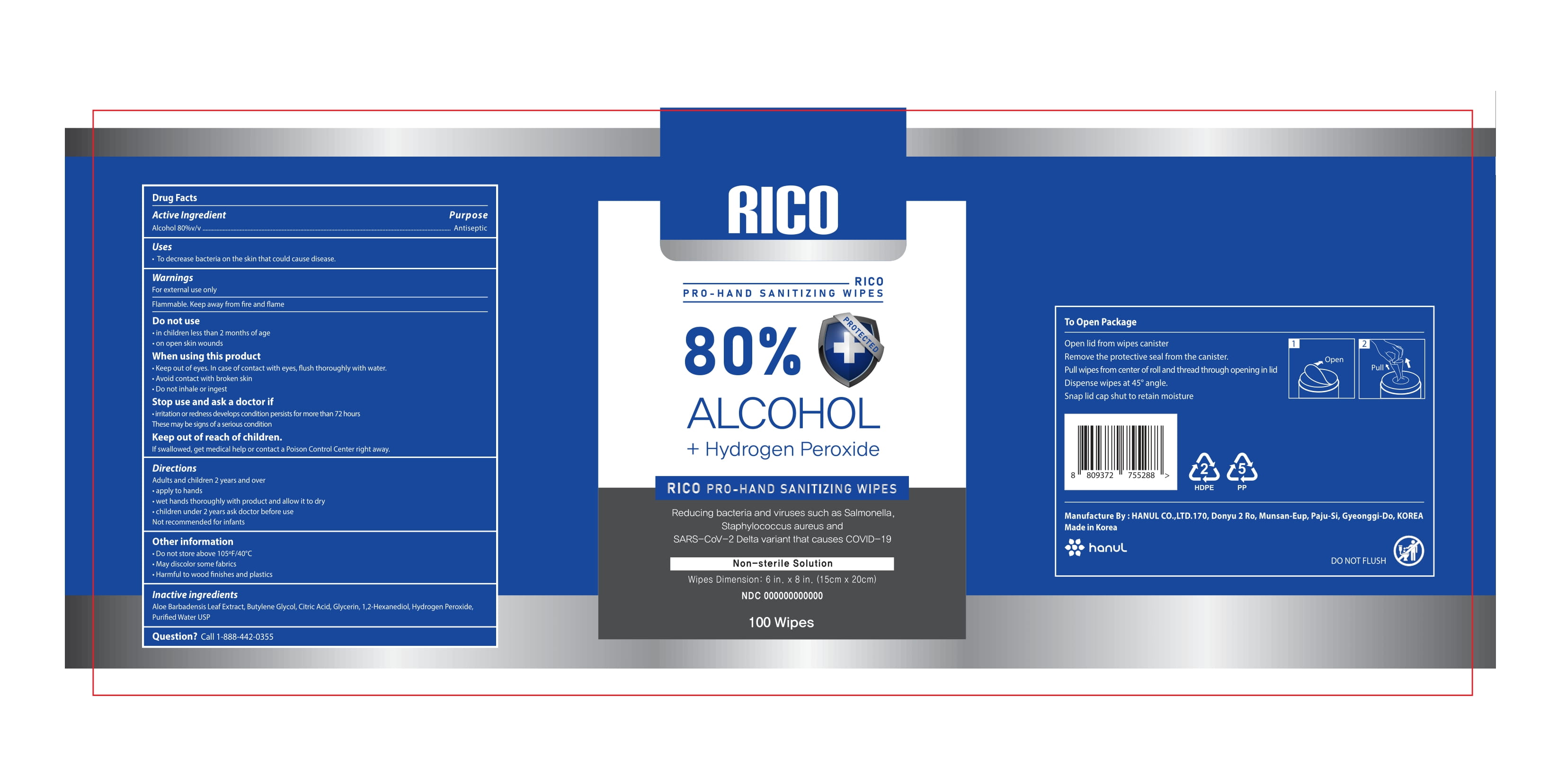 DRUG LABEL: RICO Hand Sanitizer Wipes
NDC: 75214-900 | Form: CLOTH
Manufacturer: HANUL CO.,LTD
Category: otc | Type: HUMAN OTC DRUG LABEL
Date: 20250120

ACTIVE INGREDIENTS: ALCOHOL 80 mL/100 mL
INACTIVE INGREDIENTS: GLYCERIN; HYDROGEN PEROXIDE; WATER; ALOE VERA LEAF; CITRIC ACID MONOHYDRATE; 1,2-HEXANEDIOL; BUTYLENE GLYCOL

RICO PRO-HAND SANITIZING WIPS 80% ALCOHOL + Hydrogen Peroxide

Active Ingredient(s)

Ethyl Alcohol 80% Purpose: Antiseptic

Purpose

Antiseptic, Hand Sanitizer Wipes

Use

To decrease bacteria on the skin that could cause disease

Warnings

For external use only: hands

Flammable. Keep away from fire and flame.

When using this product

keep out of eyes. In case of contact with eyes, flush thoroughly with water.

avoid contact with broken skin

do not inhale or ingest

Stop Use and ask a doctor if

irritation or redness develops

condition persists for more than 72 hours

These may be signs of a serious condition

Keep out of reach of children. If swallowed, get medical help or contact a Poison Control Center right away.

Directions

- Adults and children 2 years and over
- apply to hands
- Wet hands thoroughly with product and allow to dry
- Children under 2 years ask doctor before use
- Not recommended for infants

Other information

do not store above 105ºF/40°C

may discolor some fabrics

harmful to wood finishes and plastics

Inactive ingredients

Aloe Barbadensis Leaf Extract, Butylene Glycol, Citric Acid, Purified water USP, glycerin, hydrogen peroxide,1,2 Hexanediol,

Package Label - Principal Display Panel

NDC: 75214-900-01

RICO HAND SANITIZING WIPES 80 % ALCOHOL + HYDROGEN PEROXIDE

[“Reducing bacteria and viruses such as Salmonella, Staphylococcus aureus and SARS-CoV-2 Delta variant that causes COVID-19”

NON STERILE SOLUTION

100 wipes

wipes dimension 6in. x 8 In (15cm x 20m)